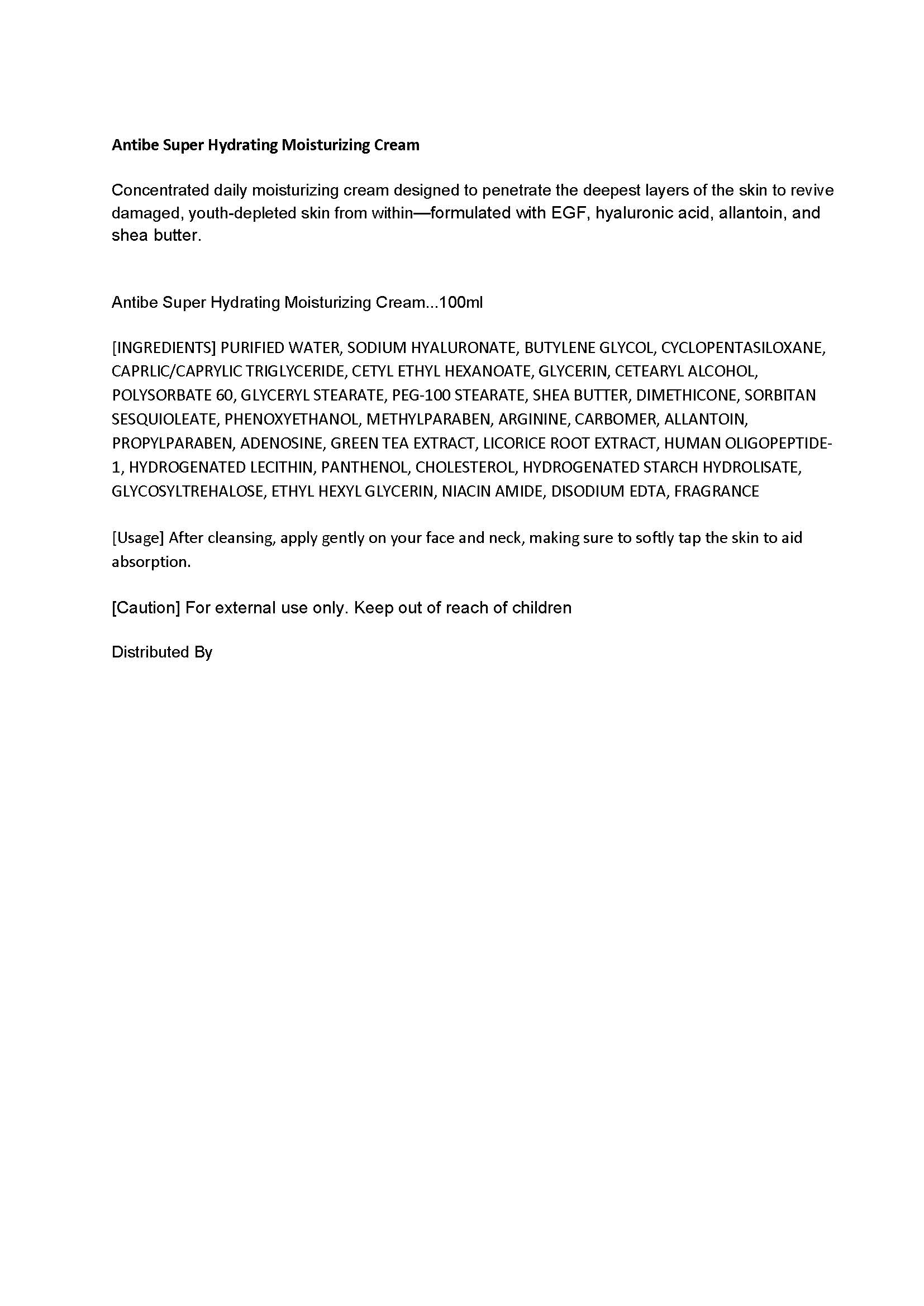 DRUG LABEL: Antibe Super Hydrating Moisturizing Cream
NDC: 70929-0001 | Form: CREAM
Manufacturer: Modongee Co., Ltd.
Category: otc | Type: HUMAN OTC DRUG LABEL
Date: 20160822

ACTIVE INGREDIENTS: ADENOSINE 0.04 g/100 mL
INACTIVE INGREDIENTS: WATER; GLYCERIN; ALLANTOIN

Drug Facts

ACTIVE INGREDIENT

ADENOSINE

INACTIVE INGREDIENT

PURIFIED WATER, SODIUM HYALURONATE, BUTYLENE GLYCOL, CYCLOPENTASILOXANE, CAPRLIC/CAPRYLIC TRIGLYCERIDE, CETYL ETHYL HEXANOATE, GLYCERIN, CETEARYL ALCOHOL, POLYSORBATE 60, GLYCERYL STEARATE, PEG-100 STEARATE, SHEA BUTTER, DIMETHICONE, SORBITAN SESQUIOLEATE, PHENOXYETHANOL, METHYLPARABEN, ARGININE, CARBOMER, ALLANTOIN, PROPYLPARABEN, GREEN TEA EXTRACT, LICORICE ROOT EXTRACT, HUMAN OLIGOPEPTIDE-1, HYDROGENATED LECITHIN, PANTHENOL, CHOLESTEROL, HYDROGENATED STARCH HYDROLISATE, GLYCOSYLTREHALOSE, ETHYL HEXYL GLYCERIN, NIACIN AMIDE, DISODIUM EDTA, FRAGRANCE

PURPOSE

Concentrated daily moisturizing cream designed to penetrate the deepest layers of the skin to revive damaged, youth-depleted skin from within—formulated with EGF, hyaluronic acid, allantoin, and shea butter.

keep out or reach of the children

INDICATIONS AND USAGE

After cleansing, apply gently on your face and neck, making sure to softly tap the skin to aid absorption.

WARNINGS

1. Do not use in the following cases(Eczema and scalp wounds)
2.Side Effects
1)Due to the use of this druf if rash, irritation, itching and symptopms of hypersnesitivity occur dicontinue use and consult your phamacisr or doctor
3.General Precautions
1)If in contact with the eyes, wash out thoroughty with water If the symptoms are servere, seek medical advice immediately
2)This product is for exeternal use only. Do not use for internal use
4.Storage and handling precautions
1)If possible, avoid direct sunlight and store in cool and area of low humidity
2)In order to maintain the quality of the product and avoid misuse
3)Avoid placing the product near fire and store out in reach of children

DOSAGE AND ADMINISTRATION

for external use only